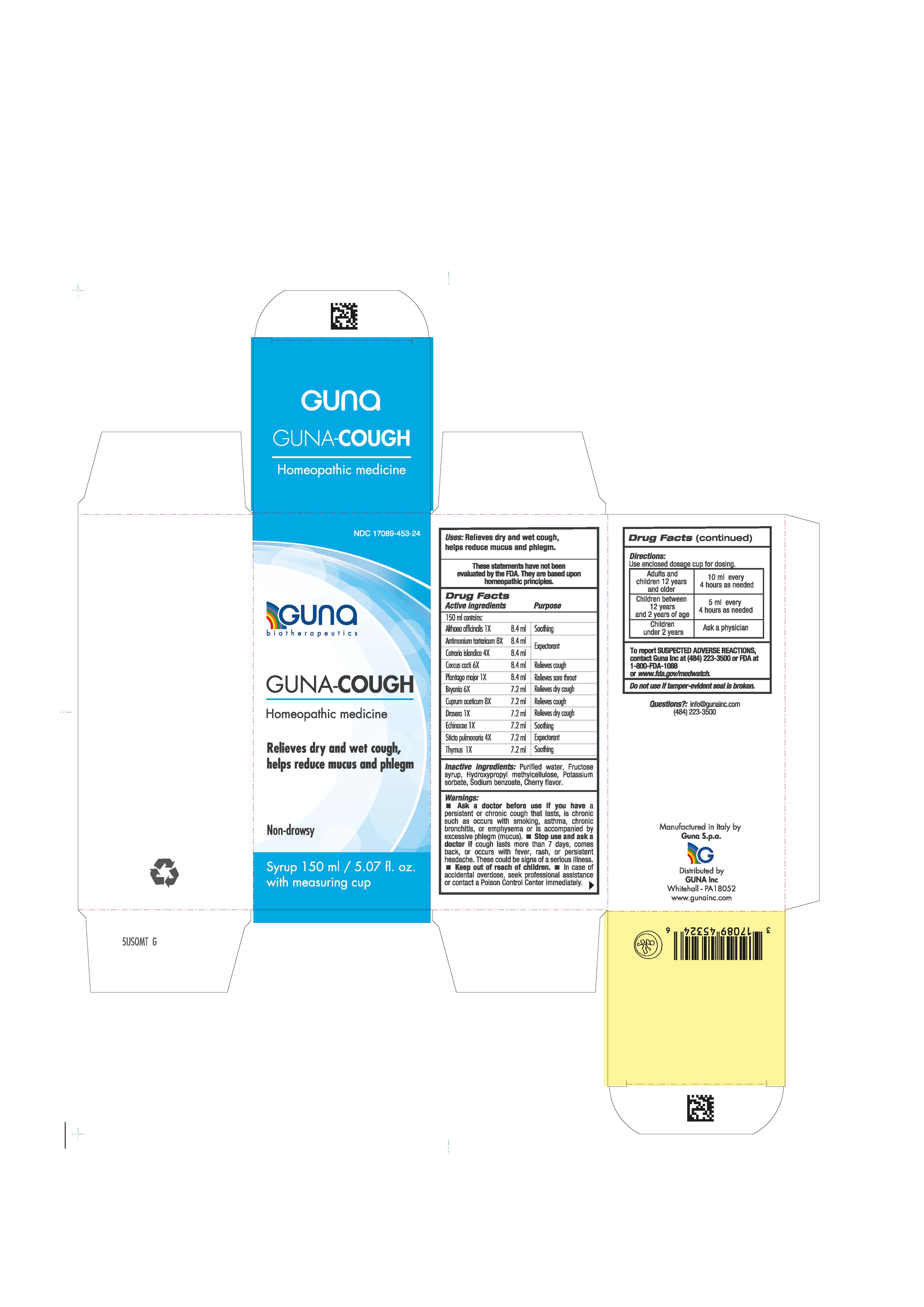 DRUG LABEL: GUNA-COUGH
NDC: 17089-453 | Form: SOLUTION/ DROPS
Manufacturer: Guna spa
Category: homeopathic | Type: HUMAN OTC DRUG LABEL
Date: 20201023

ACTIVE INGREDIENTS: ALTHAEA OFFICINALIS LEAF 1 [hp_X]/150 mL; ANTIMONY POTASSIUM TARTRATE 8 [hp_X]/150 mL; BRYONIA ALBA ROOT 6 [hp_X]/150 mL; CETRARIA ISLANDICA SUBSP. ISLANDICA 4 [hp_X]/150 mL; COCHINEAL 6 [hp_X]/150 mL; COPPER 8 [hp_X]/150 mL; DROSERA ROTUNDIFOLIA 1 [hp_X]/150 mL; ECHINACEA ANGUSTIFOLIA 1 [hp_X]/150 mL; PLANTAGO MAJOR 1 [hp_X]/150 mL; LOBARIA PULMONARIA 4 [hp_X]/150 mL; THYME 1 [hp_X]/150 mL
INACTIVE INGREDIENTS: FRUCTOSE 22.5 mL/150 mL; HYPROMELLOSES 2.25 mL/150 mL; POTASSIUM SORBATE 0.15 mL/150 mL; SODIUM BENZOATE 0.15 mL/150 mL

GUNA-COUGH

ACTIVE INGREDIENTS/PURPOSE

ALTHAEA OFFICINALIS 1X SOOTHING
ANTIMONIUM TARTARICUM 8X EXPECTORANT

CETRARIA ISLANDICA 4X EXPECTORANT

COCCUS CACTI 6X RELIEVES COUGH

PLANTAGO MAJOR 1X RELIEVES SORE THROAT

BRYONIA 6X RELIEVES DRY COUGH
CUPRUM ACETICUM 8X RELIEVES COUGH
DROSERA 1X RELIEVES DRY COUGH
ECHINACEA 1X SOOTHING
STICTA PULMONARIA 4X EXPECTORANT
THYME 1X SOOTHING

USES

- Relieves dry and wet cough
- Helps reduce mucus and phlegm

WARNINGS

Ask a doctor before use if you have a persistent or chronic cough that lasts, is chronic such as occurs with smoking, asthma, chronic bronchitis, or emphysema or is accompanied by excessive phlegm (mucus).

Stop use and ask a doctor if cough lasts more than 7 days, comes back, or occurs with fever, rash, or persistent headache. These could be signs of a serious illness.
If pregnant or breast-feeding ask a health care professional before use.
Keep out of reach of children.
In case of accidental overdose, seek professional assistance or contact a Poison Control Center immediately

PREGNANCY

If pregnant or breast-feeding ask a doctor before use

WARNINGS

Keep this and all medicines out of reach of children

DIRECTIONS

Use enclosed dosage cup for dosing
Adults and children 12 years and older 10 ml every 4 hours as needed
Children between 12 years and 2 years of age 5 ml every 4 hours as needed
Children under 2 years Ask a physician

QUESTIONS

Questions?: info@gunainc.com
Tel. (484) 223-3500

INDICATIONS AND USAGE

Directions: use enclosed cup for dosing.

INACTIVE INGREDIENT

Inactive ingredients: purified water, fructose syrup, hydroxypropyl methylcellulose, potassium sorbate, sodium benzoate, cherry flavor.